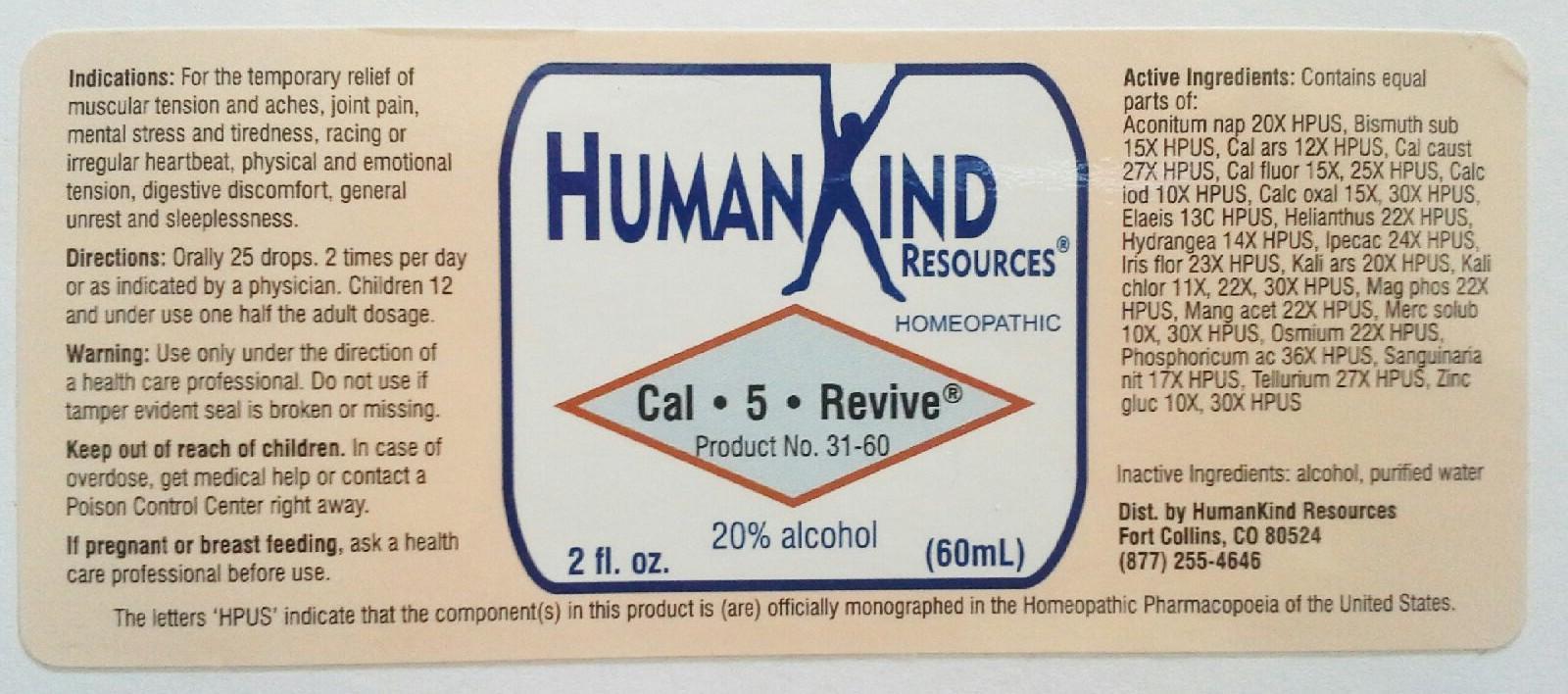 DRUG LABEL: Cal-5-Revive
NDC: 64616-109 | Form: LIQUID
Manufacturer: Vitality Works, Inc.
Category: homeopathic | Type: HUMAN OTC DRUG LABEL
Date: 20251217

ACTIVE INGREDIENTS: ACONITUM NAPELLUS 20 [hp_X]/1 mL; BISMUTH SUBNITRATE 15 [hp_X]/1 mL; CALCIUM ARSENATE 12 [hp_X]/1 mL; CALCIUM HYDROXIDE 27 [hp_X]/1 mL; CALCIUM FLUORIDE 25 [hp_X]/1 mL; CALCIUM IODIDE 10 [hp_X]/1 mL; CALCIUM OXALATE MONOHYDRATE 30 [hp_X]/1 mL; ELAEIS GUINEENSIS FRUIT 20 [hp_X]/1 mL; HELIANTHUS ANNUUS FLOWERING TOP 22 [hp_X]/1 mL; HYDRANGEA ARBORESCENS ROOT 14 [hp_X]/1 mL; IPECAC 24 [hp_X]/1 mL; IRIS GERMANICA VAR. FLORENTINA ROOT 23 [hp_X]/1 mL; POTASSIUM ARSENITE ANHYDROUS 20 [hp_X]/1 mL; POTASSIUM CHLORATE 30 [hp_X]/1 mL; MAGNESIUM PHOSPHATE, DIBASIC TRIHYDRATE 22 [hp_X]/1 mL; MANGANESE ACETATE TETRAHYDRATE 22 [hp_X]/1 mL; MERCURIUS SOLUBILIS 30 [hp_X]/1 mL; OSMIUM 22 [hp_X]/1 mL; PHOSPHORIC ACID 36 [hp_X]/1 mL; SANGUINARINE NITRATE 17 [hp_X]/1 mL; TELLURIUM 27 [hp_X]/1 mL; ZINC GLUCONATE 30 [hp_X]/1 mL
INACTIVE INGREDIENTS: WATER; ALCOHOL

Cal-5-Revive

Cal-5-Revive

Aconitum Mapellus 20X Helianthus annuus 22X Mercurius Solubilis 10X, 30X

Bismuthum Subritricum 15X Hydrangea arborescens 14X Osmium metallicum 22X

Calcarea arsenicica 12X Ipecacuanha 24X Phosphoricum Acidum 36X

Calcarea caustica 12X Iris florentina 23X Sanguinarirnum nitricum 17X

Calcarea fluorica 15X, 25X Kali arsenicosum 20X Tellurium metallicum 27X

Calcerea iodata 10X Kali chloricum 11X, 22X, 30X Zincum gluconicum 10X, 30X

Calcerea oxalica 15X, 30X Magnesia phosphorica 22X

Elaeis Guineensis 20X Manganum aceticum 22X

Cal-5-Revive

Alcohol, Purified Water

Cal-5-Revive

Use only under the direction of a health care professional.

Cal-5-Revive

Keep out of reach of children. In case of overdose, get medical help or conatact a Poison Control Center right away.

Cal-5-Revive

For the temporary relief of muscular tension and aches, joint pain, mental stress and tiredness, racing or irregular heartbeat, physical and emotional tension, digestive discomfort, general unrest and sleeplessness.

Cal-5-Revive

Orally 25 drops, 2 times per day or as indicated by a physician. Children 12 and under use one half the adult dosage.

Cal-5-Revive

Assists with distribution and usage of calcium.